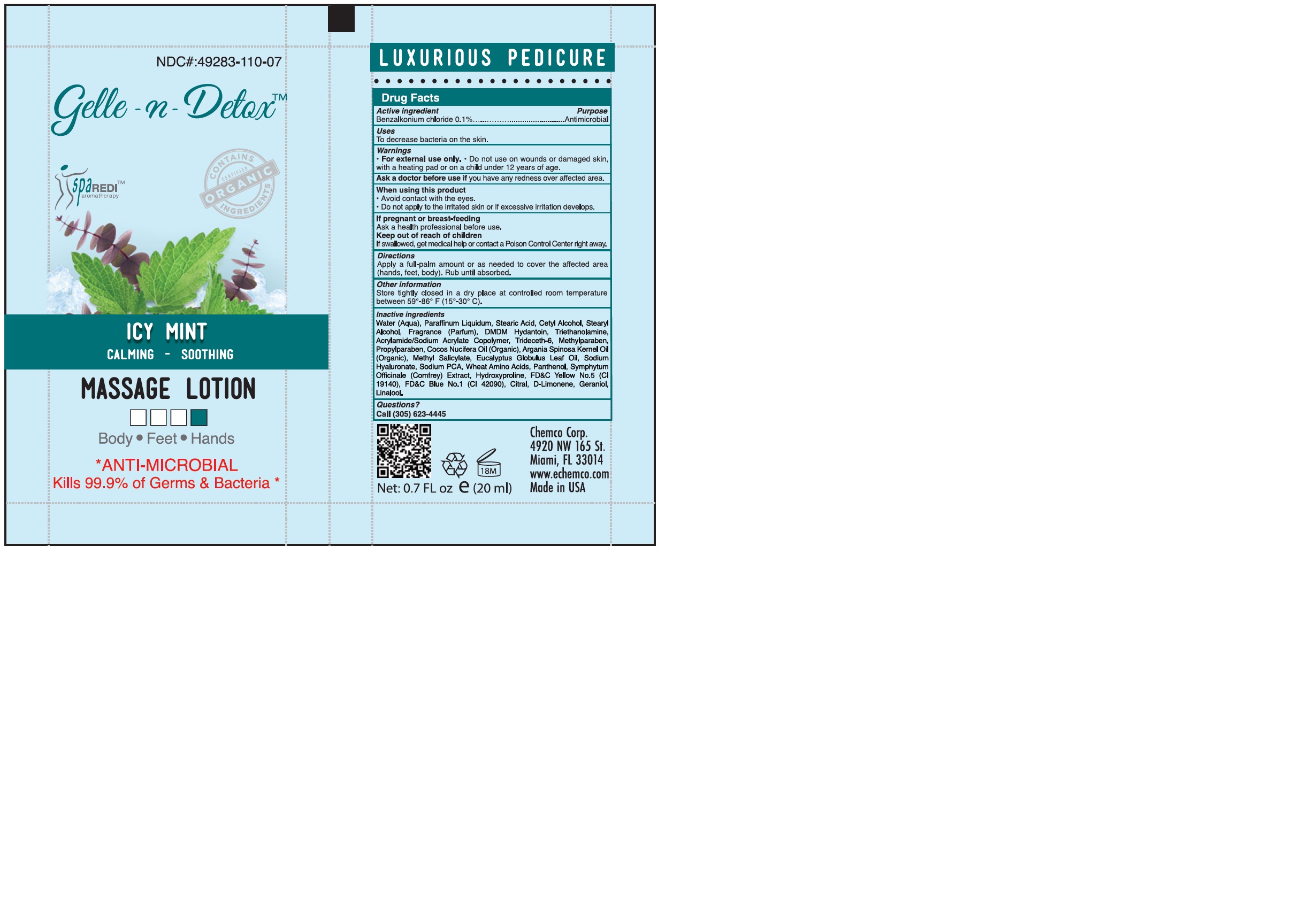 DRUG LABEL: GELLE-N-DETOX ICE MINT AND EUCALYPTUS MASSAGE
NDC: 49283-110 | Form: LOTION
Manufacturer: CHEMCO CORPORATION
Category: otc | Type: HUMAN OTC DRUG LABEL
Date: 20251205

ACTIVE INGREDIENTS: BENZALKONIUM CHLORIDE 0.1 g/100 g
INACTIVE INGREDIENTS: TRIDECETH-6; HYALURONATE SODIUM; SODIUM PYRROLIDONE CARBOXYLATE; AMINO ACIDS, WHEAT; SYMPHYTUM OFFICINALE WHOLE; FD&C BLUE NO. 1; CITRAL; LIMONENE, (+)-; WATER; STEARYL ALCOHOL; METHYL SALICYLATE; PANTHENOL; EUCALYPTUS OIL; MINERAL OIL; STEARIC ACID; TROLAMINE; PROPYLPARABEN; ARGAN OIL; FD&C YELLOW NO. 5; COCONUT OIL; METHYLPARABEN; DMDM HYDANTOIN; HYDROXYPROLINE; GERANIOL; LINALOOL, (+)-

49283-110-07

ACTIVE INGREDIENT

Benzalkonium Chloride 0.1%

PURPOSE

Antimicrobial

USES:

To decrease bacteria on the skin.

WARNINGS

For external use only.

Do not use on wounds or damaged skin, with a heating pad or on a child under 12 years of age.

WHEN USING

•Avoid contact with the eyes.
• Do not apply to the irritated skin or if excessive irritation develops.

Ask a doctor before use if you have redness over affected area.

PREGNANCY OR BREAST FEEDING

Ask a health professional before use.

KEEP OUT OF REACH OF CHILDREN

If swallowed, get medical help or contact a Poison Control Center
right away

DIRECTIONS:

Apply a full-palm amount or as needed to cover the affected area (hands, feet, body). Rub until absorbed.

OTHER SAFETY INFORMATION

Store tightly closed in a dry place at controlled room temperature between 59°-86° F (15°-30° C).

INACTIVE INGREDIENT

Water (Aqua), Paraffinum Liquidum, Stearic Acid, Cetyl Alcohol, Fragrance (Parfum), Stearyl Alcohol, DMDM Hydantoin, Triethanolamine, Acrylamide/Sodium Acrylate Copolymer, Trideceth-6, Methylparaben, Propylparaben, Cocos Nucifera Oil (Organic), Argania Spinosa Kernel Oil (Organic), Lavandula Angustifolia (Lavender) Extract, Rosmarinus Officinalis (Rosemary) Extract, Sodium Hyaluronate, Sodium PCA, Wheat Amino Acids, Panthenol, Symphytum Officinale (Comfrey) Extract, Hydroxyproline, D&C Violet No.2 (CI 60730), Benzyl Salicylate, Linalool, Hexyl Cinnamal, Alpha Isomethyl Ionone, Citronellol, Geraniol.

QUESTIONS

Call (305) 623-4445